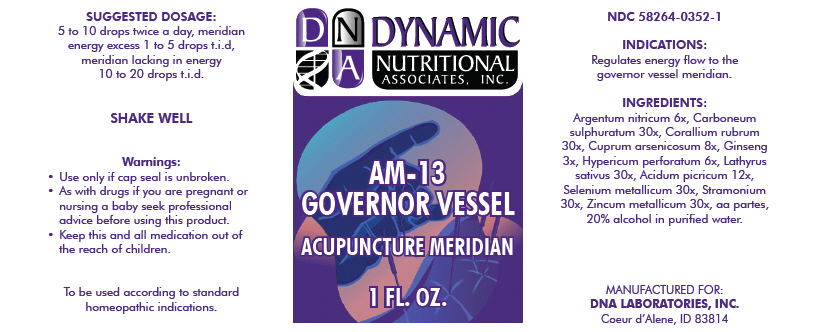 DRUG LABEL: AM-13
NDC: 58264-0352 | Form: SOLUTION
Manufacturer: DNA Labs, Inc.
Category: homeopathic | Type: HUMAN OTC DRUG LABEL
Date: 20250109

ACTIVE INGREDIENTS: CARBON DISULFIDE 30 [hp_X]/1 mL; SILVER NITRATE 6 [hp_X]/1 mL; CORALLIUM RUBRUM WHOLE 30 [hp_X]/1 mL; CUPRIC ARSENITE 8 [hp_X]/1 mL; ASIAN GINSENG 3 [hp_X]/1 mL; HYPERICUM PERFORATUM 6 [hp_X]/1 mL; LATHYRUS SATIVUS WHOLE 30 [hp_X]/1 mL; PICRIC ACID 12 [hp_X]/1 mL; SELENIUM 30 [hp_X]/1 mL; DATURA STRAMONIUM WHOLE 30 [hp_X]/1 mL; ZINC 30 [hp_X]/1 mL
INACTIVE INGREDIENTS: ALCOHOL; WATER

AM-13

NDC 58264-0352-1

INDICATIONS

PURPOSE

Regulates energy flow to the governor vessel meridian.

ACTIVE INGREDIENT

INGREDIENTS

Argentum nitricum 6x, Carboneum sulphuratum 30x, Corallium rubrum 30x, Cuprum arsenicosum 8x, Ginseng 3x, Hypericum perforatum 6x, Lathyrus sativus 30x, Acidum picricum 12x, Selenium metallicum 30x, Stramonium 30x, Zincum metallicum 30x, aa partes, 20% alcohol in purified water.

SUGGESTED DOSAGE

5 to 10 drops twice a day, meridian energy excess 1 to 5 drops t.i.d, meridian lacking in energy 10 to 20 drops t.i.d.

STORAGE AND HANDLING

SHAKE WELL

Warnings

- Use only if cap seal is unbroken.

PREGNANCY OR BREAST FEEDING

- As with drugs if you are pregnant or nursing a baby seek professional advice before using this product.

KEEP OUT OF REACH OF CHILDREN

- Keep this and all medication out of the reach of children.

To be used according to standard homeopathic indications.

PRINCIPAL DISPLAY PANEL - 1 FL. OZ. Bottle Label

DYNAMIC
NUTRITIONAL
ASSOCIATES, INC.

AM-13
GOVERNOR VESSEL

ACUPUNCTURE MERIDIAN

1 FL. OZ.